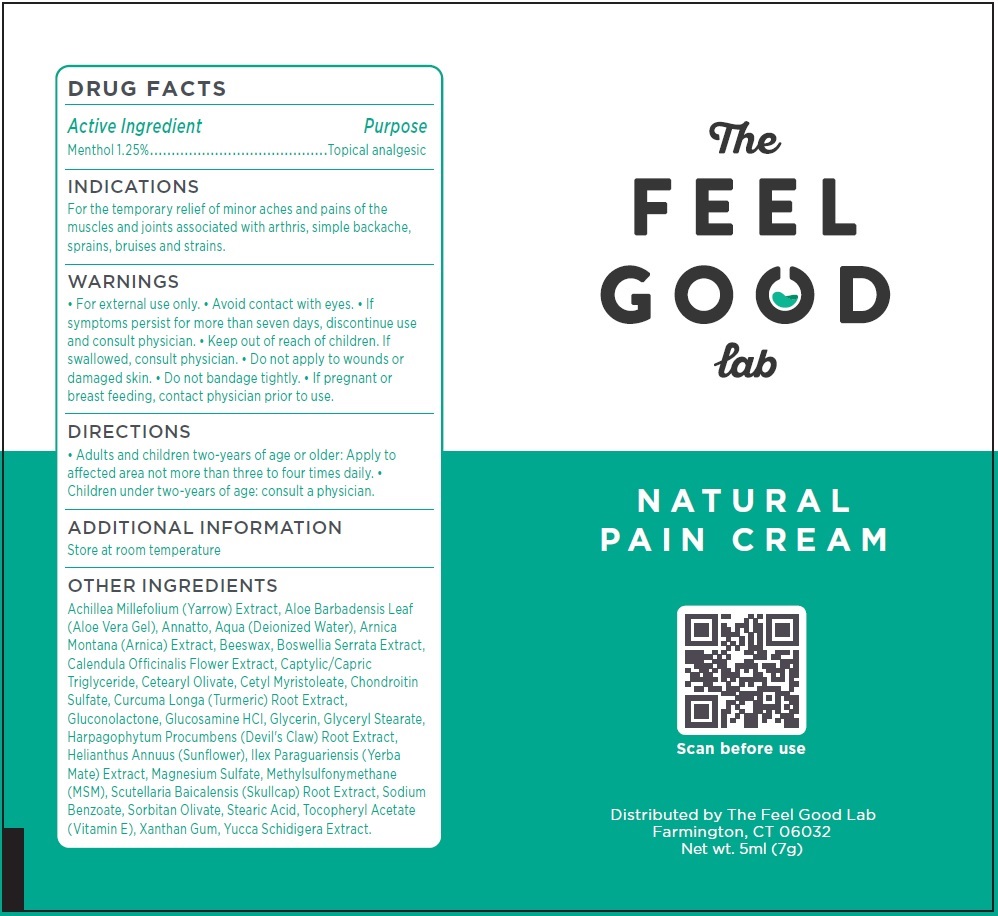 DRUG LABEL: FEEL GOOD LAB Natural Pain Cream
NDC: 70554-339 | Form: CREAM
Manufacturer: THE FEEL GOOD LAB, LLC
Category: otc | Type: HUMAN OTC DRUG LABEL
Date: 20231110

ACTIVE INGREDIENTS: MENTHOL 12.5 mg/1 mL
INACTIVE INGREDIENTS: ACHILLEA MILLEFOLIUM WHOLE; ALOE VERA LEAF; ANNATTO; WATER; ARNICA MONTANA WHOLE; YELLOW WAX; INDIAN FRANKINCENSE; CALENDULA OFFICINALIS FLOWER; MEDIUM-CHAIN TRIGLYCERIDES; CETEARYL OLIVATE; CETYL MYRISTOLEATE; TURMERIC; GLUCONOLACTONE; GLUCOSAMINE HYDROCHLORIDE; GLYCERIN; GLYCERYL MONOSTEARATE; HARPAGOPHYTUM PROCUMBENS ROOT; HELIANTHUS ANNUUS FLOWERING TOP; ILEX PARAGUARIENSIS LEAF; MAGNESIUM SULFATE, UNSPECIFIED FORM; DIMETHYL SULFONE; SCUTELLARIA BAICALENSIS ROOT; SODIUM BENZOATE; SORBITAN OLIVATE; STEARIC ACID; .ALPHA.-TOCOPHEROL ACETATE; XANTHAN GUM; YUCCA SCHIDIGERA WHOLE

FEEL GOOD LAB Natural Pain Cream

Active Ingredient

Menthol 1.25%

Purpose

Topical analgesic

INDICATIONS

For the temporary relief of minor aches and pains of the muscles and joints associated with arthris, simple backache, sprains, bruises and strains.

WARNINGS

• For external use only. • Avoid contact with eyes. • If symptoms persist for more than seven days, discontinue use and consult physician.

Keep out of reach of children.

• If swallowed, consult physician. • Do not apply to wounds or damaged skin. • Do not bandage tightly

If pregnant or breast feeding,

• contact physician prior to use.

DIRECTIONS

• Adults and children two-years of age or older: Apply to affected area not more than three to four times daily. • Children under two-years of age: consult a physician.

ADDITIONAL INFORMATION

Store at room temperature

OTHER INGREDIENTS

Achillea Millefolium (Yarrow) Extract, Aloe Barbadensis Leaf (Aloe Vera Gel), Annatto, Aqua (Deionized Water), Arnica Montana (Arnica) Extract, Beeswax, Boswellia Serrata Extract, Calendula Officinalis Flower Extract, Captylic/Capric Triglyceride, Cetearyl Olivate, Cetyl Myristoleate, Chondroitin Sulfate, Curcuma Longa (Turmeric) Root Extract, Gluconolactone, Glucosamine HCI, Glycerin, Glyceryl Stearate, Harpagophytum Procumbens (Devil's Claw) Root Extract, Helianthus Annuus (Sunflower), Ilex Paraguariensis (Yerba Mate) Extract, Magnesium Sulfate, Methylsulfonymethane (MSM), Scutellaria Baicalensis (Skullcap) Root Extract, Sodium Benzoate, Sorbitan Olivate, Stearic Acid, Tocopheryl Acetate (Vitamin E), Xanthan Gum, Yucca Schidigera Extract.